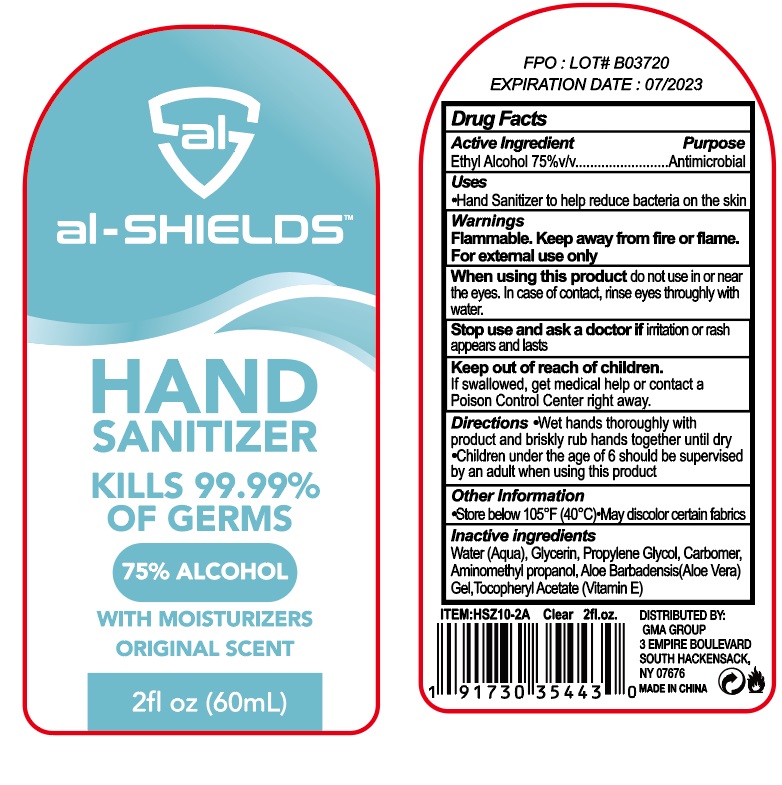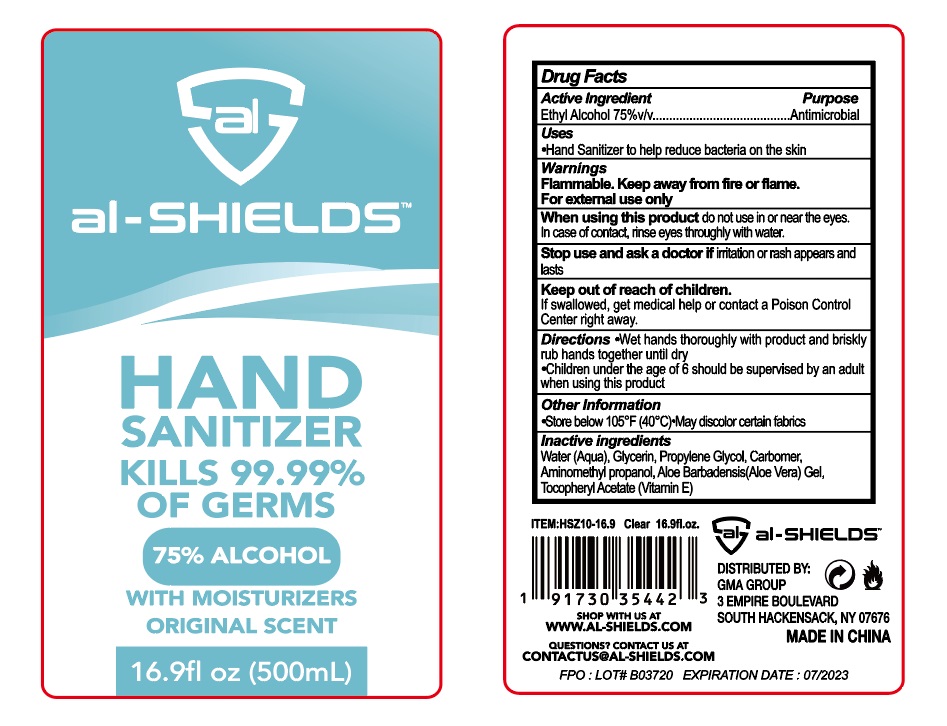 DRUG LABEL: al-SHIELDS Hand Sanitizer
NDC: 75007-005 | Form: GEL
Manufacturer: YIRONG TRADING (NANJING) CO., LTD
Category: otc | Type: HUMAN OTC DRUG LABEL
Date: 20200726

ACTIVE INGREDIENTS: ALCOHOL 75 mL/100 mL
INACTIVE INGREDIENTS: WATER; GLYCERIN; PROPYLENE GLYCOL; CARBOMER HOMOPOLYMER TYPE A (ALLYL PENTAERYTHRITOL CROSSLINKED); AMINOMETHYLPROPANOL; ALOE VERA LEAF; .ALPHA.-TOCOPHEROL ACETATE, D-

Active Ingredient

Ethyl Alcohol 75% v/v.

Purpose

Antimicrobial

Use

Hand Sanitizer to help reduce bacteria on the skin that could cause disease.

Warnings

Flammable. Keep away from fire or flame.

For external use only.

When using this product do not use in or near the eyes. In case of contact , rinse eyes thoroughly with water. Avoid using on broken skin.

Stop use and ask a doctor if irritation or rash appears and lasts.

Keep out of reach of children. If swallowed, get medical help or contact a Poison Control Center right away.

Directions

- Put enough product in your palm to cover hands and rub hands together until dry.
- Children under 6 years of age should be supervised when using this product.

Other Information

- Store below 105℉ (40℃).
- May discolor certain fabrics.

Inactive ingredients

Water (Aqua), Glycerin, Propylene Glycol, Carbomer, Aminomethyl Propanol, Aloe Barbadensis (Aloe Vera) Gel, Tocopheryl Acetate (Vitamin E)